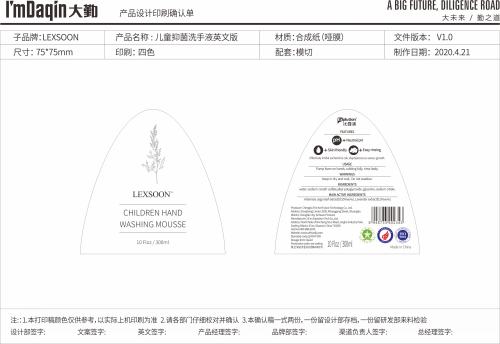 DRUG LABEL: CHILDREN HAND WASHING MOUSSE
NDC: 75709-003 | Form: LIQUID
Manufacturer: Xi'an Explution Tech Co.,Ltd.
Category: otc | Type: HUMAN OTC DRUG LABEL
Date: 20200429

ACTIVE INGREDIENTS: ARTEMISIA ARGYI LEAF 0.55 g/100 mL; LAVANDULA ANGUSTIFOLIA SUBSP. ANGUSTIFOLIA FLOWER 0.3 g/100 mL
INACTIVE INGREDIENTS: GLYCERIN; SODIUM CITRATE, UNSPECIFIED FORM; WATER

CHILDREN HAND WASHING MOUSSE

ACTIVE INGREDIENTS

Artemisia argyi leaf extract(0.55%w/w) ,Lavender extract(0.3%w/w)

USAGE

Pump foam on hands, rubbing fully, rinse lastly.

WARNINGS

Keep in dry and cool, Do not swallow.

Inactive ingredients

water,sodium coceth sulfate,alkyl polyglycoside,glycerine,sodium citrate.